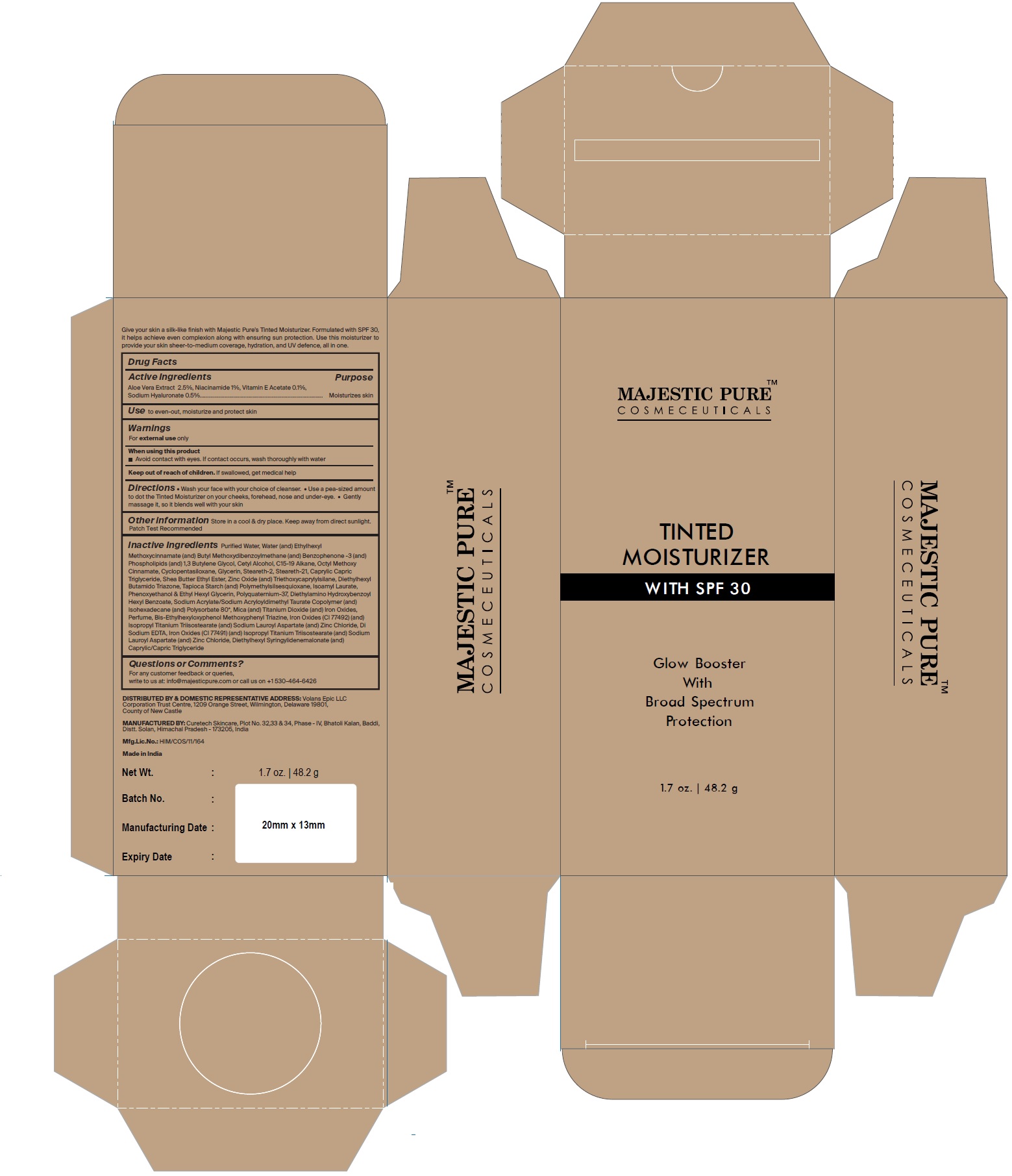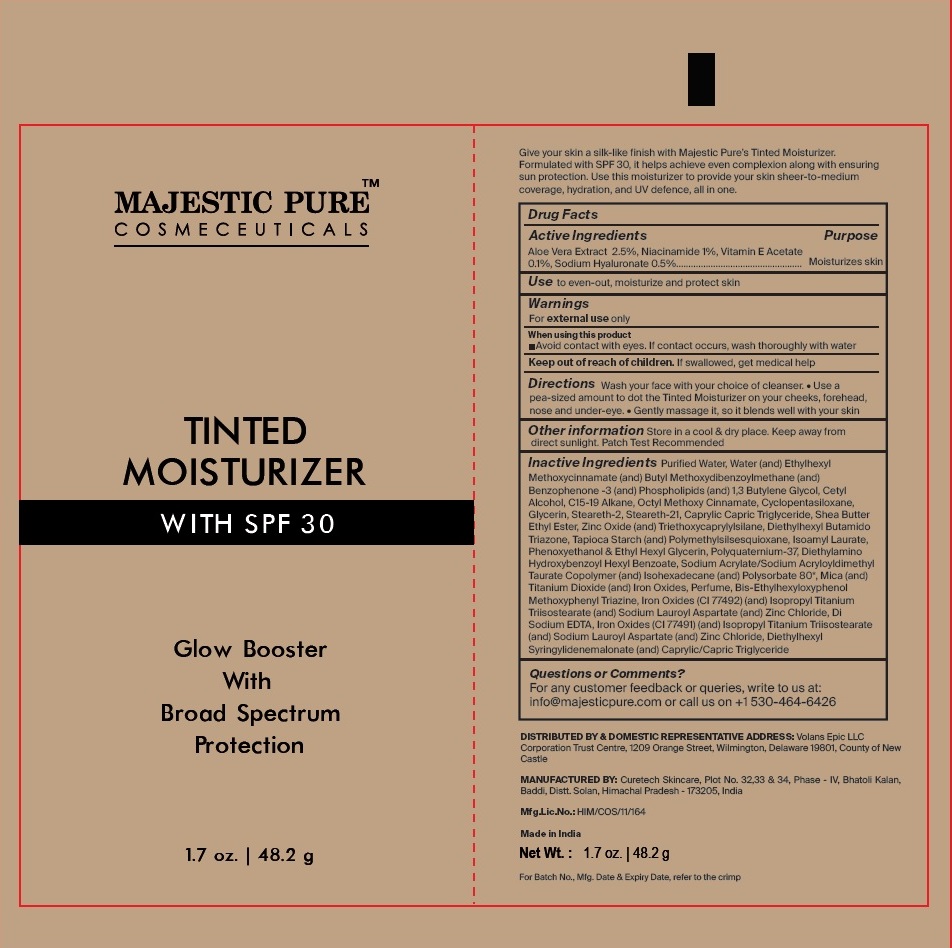 DRUG LABEL: TINTED MOISTURIZER
NDC: 83325-006 | Form: CREAM
Manufacturer: Volans Epic LLC
Category: otc | Type: HUMAN OTC DRUG LABEL
Date: 20231021

ACTIVE INGREDIENTS: ALOE VERA LEAF 1.205 g/48.2 g; NIACINAMIDE 0.482 g/48.2 g; .ALPHA.-TOCOPHEROL ACETATE 0.0482 g/48.2 g; HYALURONATE SODIUM 0.241 g/48.2 g
INACTIVE INGREDIENTS: WATER; OCTINOXATE; AVOBENZONE; OXYBENZONE; BUTYLENE GLYCOL; CETYL ALCOHOL; C15-19 ALKANE; CYCLOMETHICONE 5; GLYCERIN; STEARETH-2; STEARETH-21; MEDIUM-CHAIN TRIGLYCERIDES; SHEA BUTTER ETHYL ESTERS; ZINC OXIDE; TRIETHOXYCAPRYLYLSILANE; ISCOTRIZINOL; STARCH, TAPIOCA; POLYMETHYLSILSESQUIOXANE (4.5 MICRONS); ISOAMYL LAURATE; DIETHYLAMINO HYDROXYBENZOYL HEXYL BENZOATE; SODIUM ACRYLATE; ISOHEXADECANE; POLYSORBATE 80; MICA; TITANIUM DIOXIDE; BEMOTRIZINOL; ISOPROPYL TITANIUM TRIISOSTEARATE; SODIUM LAUROYL ASPARTATE; ZINC CHLORIDE; EDETATE DISODIUM ANHYDROUS; DIETHYLHEXYL SYRINGYLIDENEMALONATE; FERRIC OXIDE YELLOW; FERRIC OXIDE RED; PHENOXYETHANOL; ETHYLHEXYLGLYCERIN; SULFURYL FLUORIDE; LECITHIN, SOYBEAN

MAJESTIC PURETM
COSMECEUTICALS
TINTED
MOISTURIZER
WITH SPF 30
Glow Booster With Broad Spectrum Protection
1.7 oz. | 48.2 g

Give your skin a silk-like finish with Majestic Pure's Tinted Moisturizer. Formulated with SPF 30, it helps achieve even complexion along with ensuring sun protection. Use this moisturizer to provide your skin sheer-to-medium coverage, hydration, and UV defence, all in one.

Drug Facts

Active Ingredients Purpose

Aloe Vera Extract 2.5%, Niacinamide 1%, Vitamin E Acetate

0.1%, Sodium Hyaluronate 0.5%................................................... Moisturizes skin

Useto even-out, moisturize and protect skin

Warnings

For external useonly

When using this product

Avoid contact with eyes. If contact occurs, wash thoroughly with water

Keep out of reach of children.If swallowed, get medical help

DirectionsWash your face with your choice of cleanser. • Use a pea-sized amount to dot the Tinted Moisturizer on your cheeks, forehead, nose and under-eye. • Gently massage it, so it blends well with your skin

Other informationStore in a cool & dry place. Keep away from direct sunlight. Patch Test Recommended

INACTIVE INGREDIENT

Inactive IngredientsPurified Water, Water (and) Ethylhexyl Methoxycinnamate (and) Butyl Methoxydibenzoylmethane (and) Benzophenone -3 (and) Phospholipids (and) 1,3 Butylene Glycol, Cetyl Alcohol, C15-19 Alkane, Octyl Methoxy Cinnamate, Cyclopentasiloxane, Glycerin, Steareth-2, Steareth-21, Caprylic Capric Triglyceride, Shea Butter Ethyl Ester, Zinc Oxide (and) Triethoxycaprylylsilane, Diethylhexyl Butamido Triazone, Tapioca Starch (and) Polymethylsilsesquioxane, Isoamyl Laurate, Phenoxyethanol & Ethyl Hexyl Glycerin, Polyquaternium-37, Diethylamino Hydroxybenzoyl Hexyl Benzoate, Sodium Acrylate/Sodium Acryloyldimethyl Taurate Copolymer (and) Isohexadecane (and) Polysorbate 80*, Mica (and) Titanium Dioxide (and) Iron Oxides, Perfume, Bis-Ethylhexyloxyphenol Methoxyphenyl Triazine, Iron Oxides (CI 77492) (and) Isopropyl Titanium Triisostearate (and) Sodium Lauroyl Aspartate (and) Zinc Chloride, Di Sodium EDTA, Iron Oxides (CI 77491) (and) Isopropyl Titanium Triisostearate (and) Sodium Lauroyl Aspartate (and) Zinc Chloride, Diethylhexyl Syringylidenemalonate (and) Caprylic/Capric Triglyceride

Questions or Comments?

For any customer feedback or queries, write to us at: info@majesticpure.com or call us on +1 530-464-6426

DISTRIBUTED BY & DOMESTIC REPRESENTATIVE ADDRESS: Volans Epic LLC Corporation Trust Centre, 1209 Orange Street, Wilmington, Delaware 19801, County of New Castle

MANUFACTURED BY: Curetech Skincare, Plot No. 32,33 & 34, Phase - IV, Bhatoli Kalan, Baddi, Distt. Solan, Himachal Pradesh - 173205, India

Mfg.Lic.No.: HIM/COS/11/164

Made in India

Net Wt. : 1.7 oz. | 48.2 g

For Batch No., Mfg. Date & Expiry Date, refer to the crimp

PACKAGE LABEL.PRINCIPAL DISPLAY PANEL

Tinted Moisturizer with SPF 30 Tube Label

Tinted Moisturizer with SPF 30 Carton Label